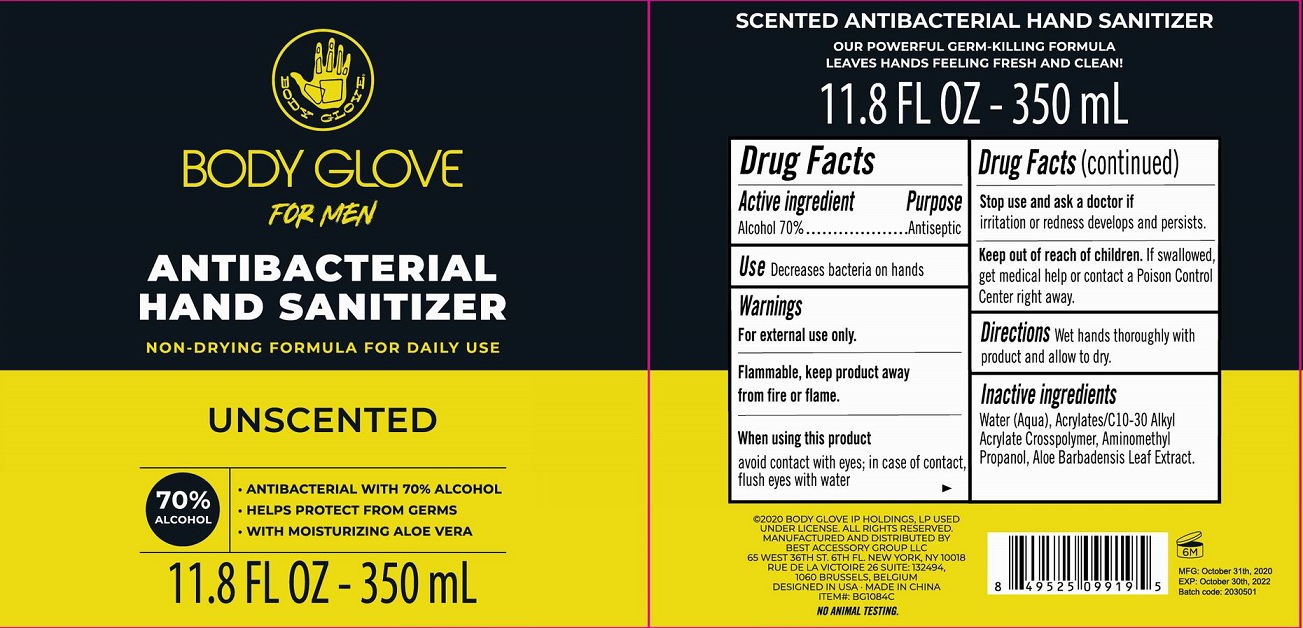 DRUG LABEL: Body Glove For Men Antibacterial Hand Sanitizer Unscented
NDC: 56136-498 | Form: LIQUID
Manufacturer: Ganzhou Olivee Cosmetic Co., Ltd.
Category: otc | Type: HUMAN OTC DRUG LABEL
Date: 20201113

ACTIVE INGREDIENTS: ALCOHOL 70 mL/100 mL
INACTIVE INGREDIENTS: WATER; CARBOMER COPOLYMER TYPE A; AMINOMETHYL PROPANEDIOL; ALOE VERA LEAF

Hand sanitizer

Active ingredient

Alcohol 70%

Purpose

Antibacterial

Use

Decreases bacteria on hands

Warnings

For external use only.

Flammbale, Keep product away from fire or flame.

When using this product

avoid contact with eyes; in case of contact, flush eyes with water.

Stop use and ask a doctor if

- irritation and redness develops and persists.

Keep out of reach of children.

If swallowed, get medical help or contact a Poison Control Center right away.

Directions

Wet hands thoroughly with product and allow to dry.

Inactive ingredients

Water (Aqua), Acrylates/C10-30 Alkyl Acrylate Crosspolymer, Aminomethyl Propanol, Aloe Barbadensis Leaf Extract.